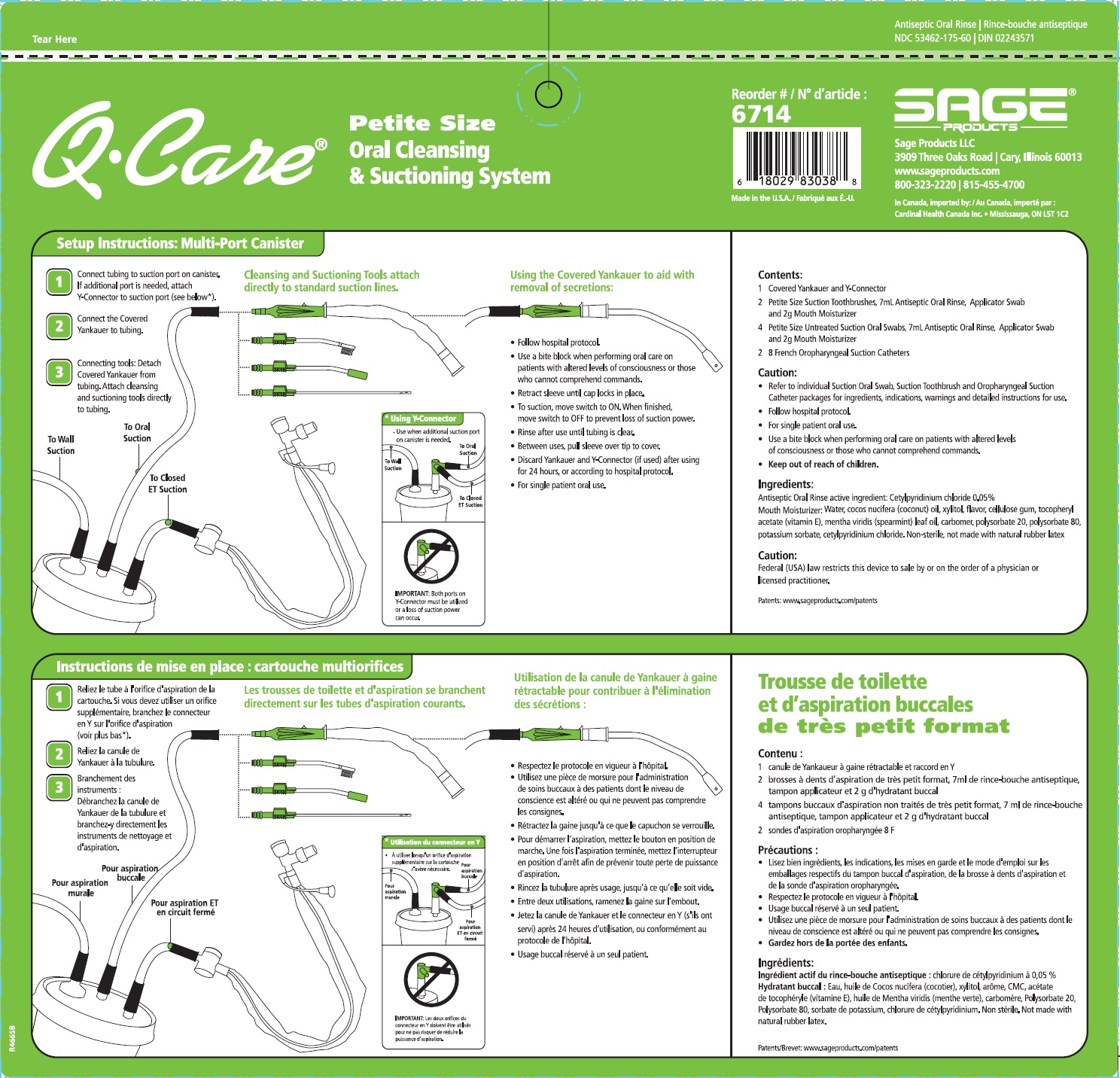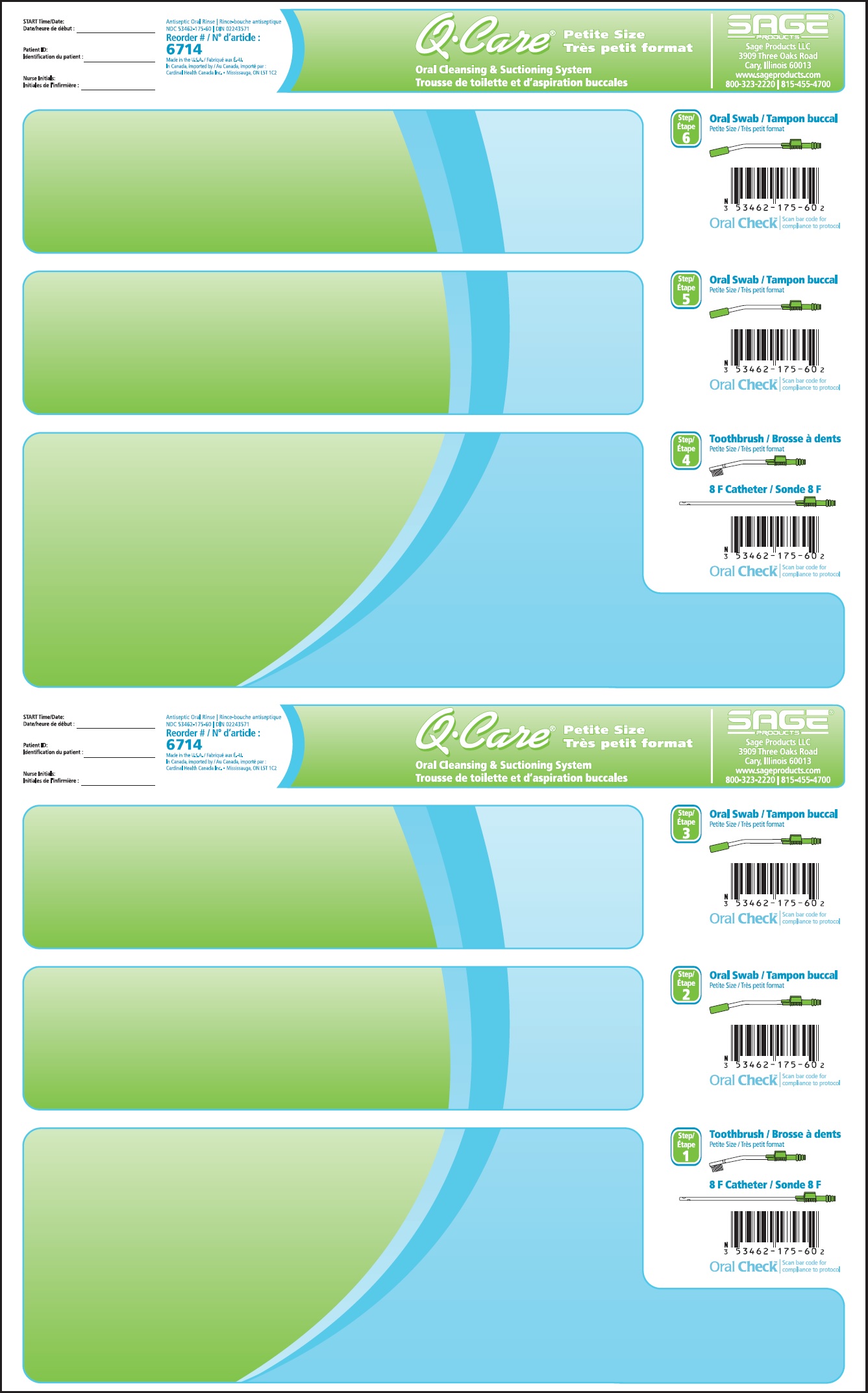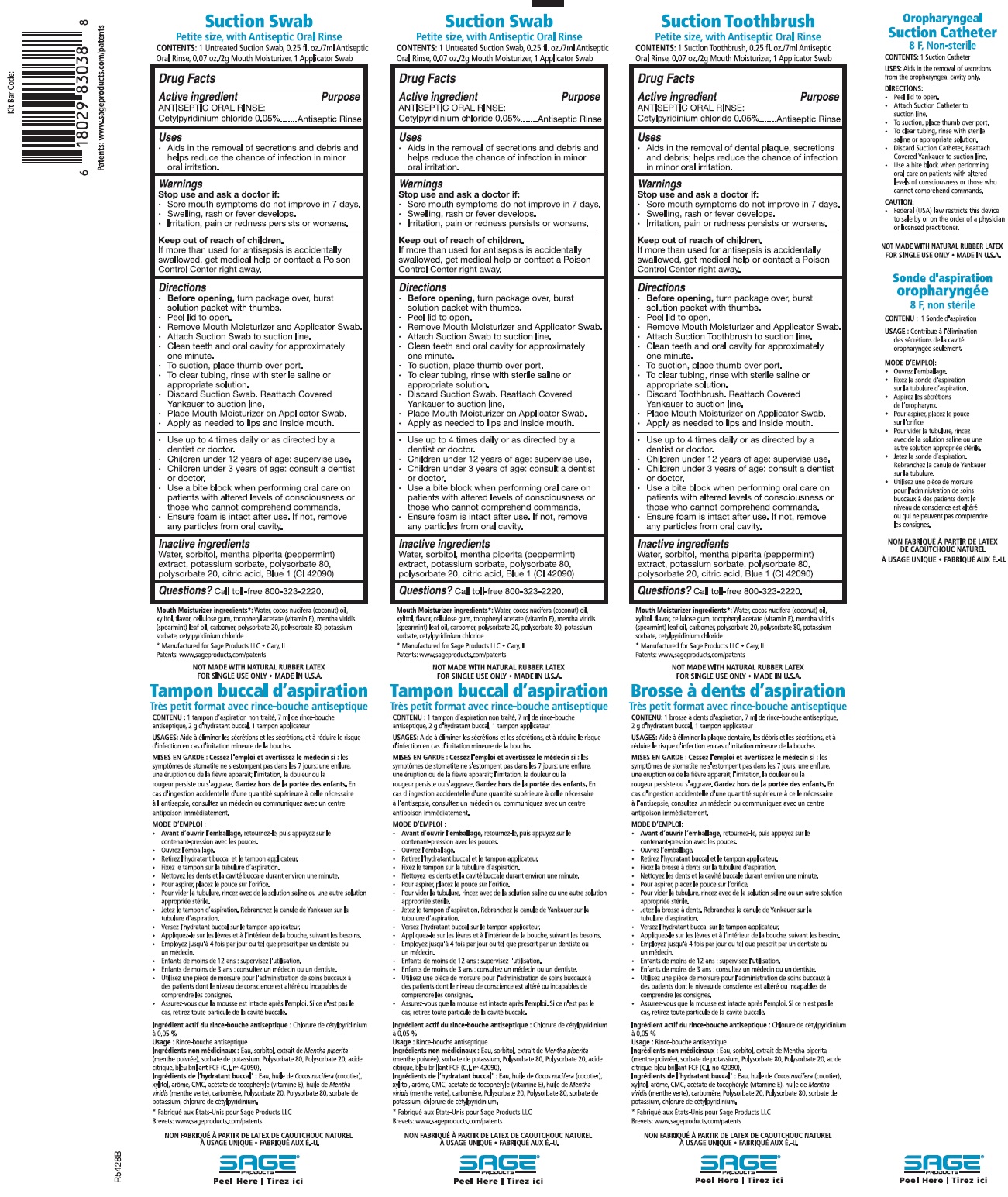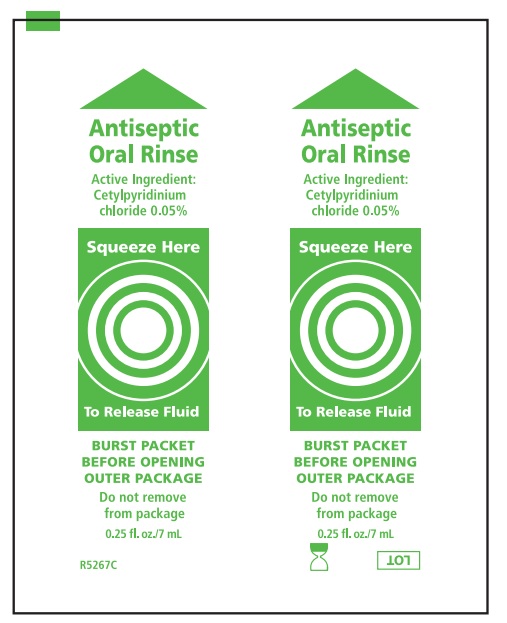 DRUG LABEL: QCare Petite Size Oral Cleansing and Suctioning System
NDC: 53462-714 | Form: KIT | Route: BUCCAL
Manufacturer: Sage Products, LLC
Category: otc | Type: HUMAN OTC DRUG LABEL
Date: 20190117

ACTIVE INGREDIENTS: CETYLPYRIDINIUM CHLORIDE 0.5 mg/1 mL
INACTIVE INGREDIENTS: SORBITOL; POTASSIUM SORBATE; POLYSORBATE 80; POLYSORBATE 20; CITRIC ACID MONOHYDRATE; FD&C BLUE NO. 1; WATER

QCare Petite Size Oral Cleansing and Suctioning System

Drug Facts

Suction Swab, Petite Size, with Antiseptic Oral Rinse/Suction Toothbrush, Petite Size, with Antiseptic Oral Rinse
Active Ingredient: ANTISEPTIC ORAL RINSE: | Purpose
Cetylpyridinium chloride .05% | Antiseptic Rinse

Uses

Suction Swab with Antiseptic Oral Rinse
- Aids in the removal of secretions and debris and helps reduce the chance of infection in minor oral irritation.

Suction Toothbrush with Antiseptic Oral Rinse
- Aids in the removal of dental plaque, secretions, and debris; helps reduce the chance of infection in minor oral irritation.

Oropharyngeal Suction Catheter
- Aids in the removal of secretions from the oropharyngeal cavity only.

Warnings

Stop use and ask a doctor if:
- Sore mouth symptoms do not improve in 7 days.
- Swelling, rash or fever develops.
- Irritation, pain or redness persists or worsens.

Keep out of reach of children.
If more than used for antisepsis is accidentally swallowed, get medical help or contact a Poison Control Center right away.

DIRECTIONS

Suction Swab with Antiseptic Oral Rinse

- Before opening, turn package over, burst solution packet with thumbs.
- Peel lid to open.
- Remove Mouth Moisturizer and Applicator Swab.
- Attach Suction Swab to suction line.
- Clean teeth and oral cavity for approximately one minute.
- To suction, place thumb over port.
- To clear tubing, rinse with sterile saline or appropriate solution.
- Discard Suction Swab. Reattach Covered Yankauer to suction line.
- Place Mouth Moisturizer on Applicator Swab.
- Apply as needed to lips and inside mouth.

- Use up to 4 times daily or as directed by a dentist or doctor.
- Children under 12 years of age: supervise use.
- Children under 3 years of age: consult a dentist or doctor.
- Use a bite block when performing oral care on patients with altered levels of consciousness or those who cannot comprehend commands.
- Ensure foam is intact after use. If not, remove any particles from oral cavity.

Suction Toothbrush with Antiseptic Oral Rinse

- Before opening, turn package over, burst solution packet with thumbs.
- Peel lid to open.
- Remove Mouth Moisturizer and Applicator Swab.
- Attach Suction Toothbrush to suction line.
- Clean teeth and oral cavity for approximately one minute.
- To suction, place thumb over port.
- To clear tubing, rinse with sterile saline or appropriate solution.
- Discard Toothbrush. Reattach Covered Yankauer to suction line.
- Place Mouth Moisturizer on Applicator Swab.
- Apply as needed to lips and inside mouth.

- Use up to 4 times daily or as directed by a dentist or doctor.
- Children under 12 years of age: supervise use.
- Children under 3 years of age: consult a dentist or doctor.
- Use a bite block when performing oral care on patients with altered levels of consciousness or those who cannot comprehend commands.
- Ensure foam is intact after use. If not, remove any particles from oral cavity.

Oropharyngeal Suction Catheter

- Peel lid to open.
- Attach Suction Catheter to suction line.
- To suction, place thumb over port.
- To clear tubing, rinse with sterile saline or appropriate solution.
- Discard Suction Catheter. Reattach Covered Yankauer to suction line.
- Use a bite block when performing oral care on patients with altered levels of consciousness or those who cannot comprehend commands.

CAUTION:

- Federal (USA) law restricts this device to sale by or on the order of a physician or licensed practitioner.

Inactive Ingredients

Water, sorbitol, mentha piperita (peppermint) extract, potassium sorbate, polysorbate 80, polysorbate 20, citric acid, Blue 1 (CI 42090)

Questions?

Call toll-free 800-323-2220.

Mouth Moisturizer ingredients*

Water, cocos nucifera (coconut) oil, xylitol, flavor, cellulose gum, tocopheryl acetate (vitamin E), mentha veridis (spearmint) leaf oil, carbomer, polysorbate 20, polysorbate 80, potassium sorbate, cetylpyridinium chloride

* Manufactured for Sage Products LLC • Cary, IL

www.sageproducts.com/patents

NOT MADE WITH NATURAL RUBBER LATEX • FOR SINGLE USE ONLY • MADE IN USA